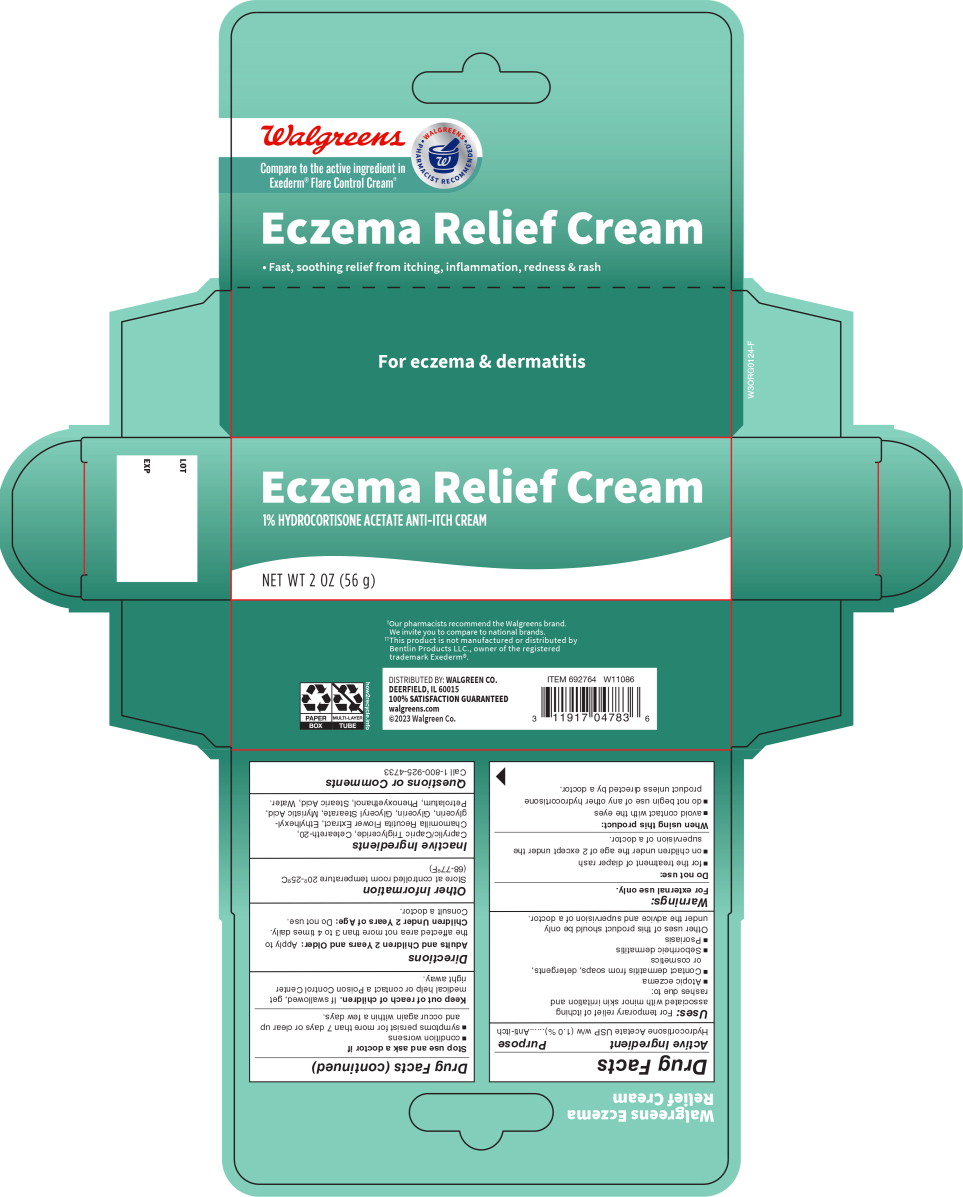 DRUG LABEL: Walgreens Eczema Relief
NDC: 0363-0357 | Form: CREAM
Manufacturer: Walgreen Co.
Category: otc | Type: HUMAN OTC DRUG LABEL
Date: 20240228

ACTIVE INGREDIENTS: HYDROCORTISONE ACETATE 10 mg/1 g
INACTIVE INGREDIENTS: MEDIUM-CHAIN TRIGLYCERIDES; POLYOXYL 20 CETOSTEARYL ETHER; CHAMOMILE; ETHYLHEXYLGLYCERIN; GLYCERIN; GLYCERYL MONOSTEARATE; MYRISTIC ACID; PETROLATUM; PHENOXYETHANOL; STEARIC ACID; WATER

Drug Facts

Active Ingredient

Hydrocortisone Acetate USP w/w (1.0 %).

Purpose

Anti-itch

Uses:

For temporary relief of itching associated with minor skin irritation and rashes due to:

- Atopic eczema
- Contact dermatitis from soaps, detergents, or cosmetics
- Seborrheic dermatitis
- Psoriasis

Other uses of this product should be only under the advice and supervision of a doctor.

Warnings:

For external use only.

Do not use:

- for the treatment of diaper rash
- on children under the age of 2 except under the supervision of a doctor.

When using this product:

- avoid contact with the eyes
- do not begin use of any other hydrocortisone product unless directed by a doctor.

Stop use and ask a doctor if

- condition worsens
- symptoms persist for more than 7 days or clear up and occur again within a few days.

Keep out of reach of children. If swallowed, get medical help or contact a Poison Control Center right away.

Directions

Adults and Children 2 Years and Older: Apply to the affected area not more than 3 to 4 times daily.

Children Under 2 Years of Age: Do not use. Consult a doctor.

Other Information

Store at controlled room temperature 20º-25ºC (68-77ºF)

Inactive Ingredients

Caprylic/Capric Triglyceride, Ceteareth-20, Chamomilla Recutita Flower Extract, Ethylhexylglycerin, Glycerin, Glyceryl Stearate, Myristic Acid, Petrolatum, Phenoxyethanol, Stearic Acid, Water.

Questions or Comments

Call 1-800-925-4733

Principal Display Panel – 56 g Carton Label

Walgreens

Compare to the active ingredient in
Exederm® Flare Control Cream††

WALGREENS PHARMACIST RECOMMENDED

Eczema Relief Cream

- Fast, soothing relief from itching, inflammation, redness & rash

For eczema & dermatitis

Eczema Relief Cream

1% HYDROCORTISONE ACETATE ANTI-ITCH CREAM

NET WT 2 OZ (56 g)